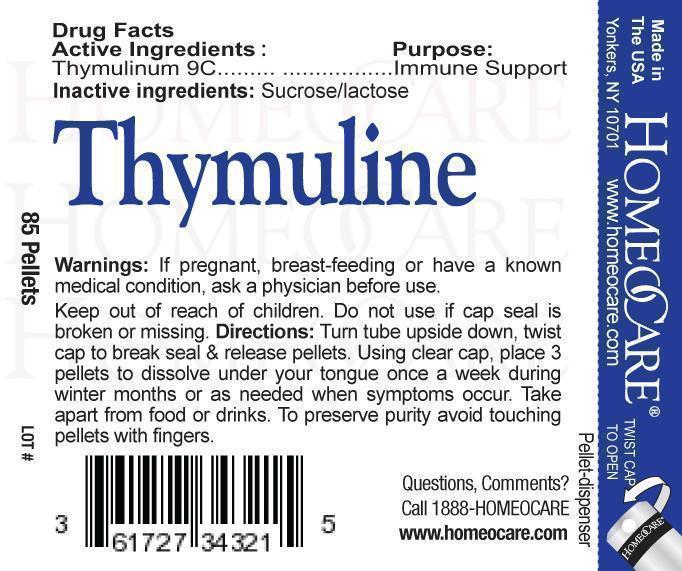 DRUG LABEL: Thymuline
NDC: 61727-343 | Form: PELLET
Manufacturer: Homeocare Laboratories
Category: homeopathic | Type: HUMAN OTC DRUG LABEL
Date: 20190228

ACTIVE INGREDIENTS: NONATHYMULIN 9 [hp_C]/4 g
INACTIVE INGREDIENTS: SUCROSE; LACTOSE

Thymuline

Active Ingredients:

Thymulinum 9C

Inactive Ingredients:

Sucrose/lactose.

Purpose:

Immune Support

Warnings:

If pregnant, breast-feeding or have a known medical condition, ask a physician before use.

Indications & Usage:

Turn tube upside down. twist cap upside down, twist cap to break seal & release pellets. Using clear cap, place 3 pellets to dissolve under your tongue once a week during winter months or as needed when symptoms occur. Take apart from food or drinks. To preserve purity avoid touching pellets with fingers.

Keep out of reach of children.

Dosage & Administration

Turn tube upside down. twist cap upside down, twist cap to break seal & release pellets. Using clear cap, place 3 pellets to dissolve under your tongue once a week during winter months or as needed when symptoms occur. Take apart from food or drinks. To preserve purity avoid touching pellets with fingers.